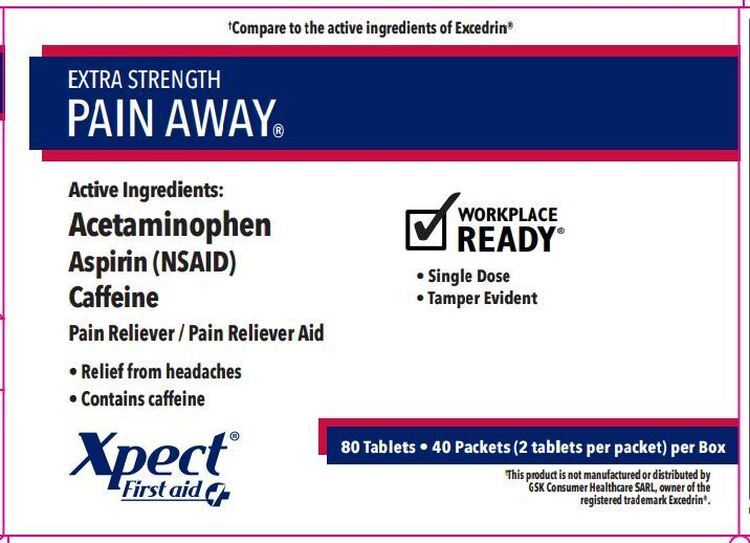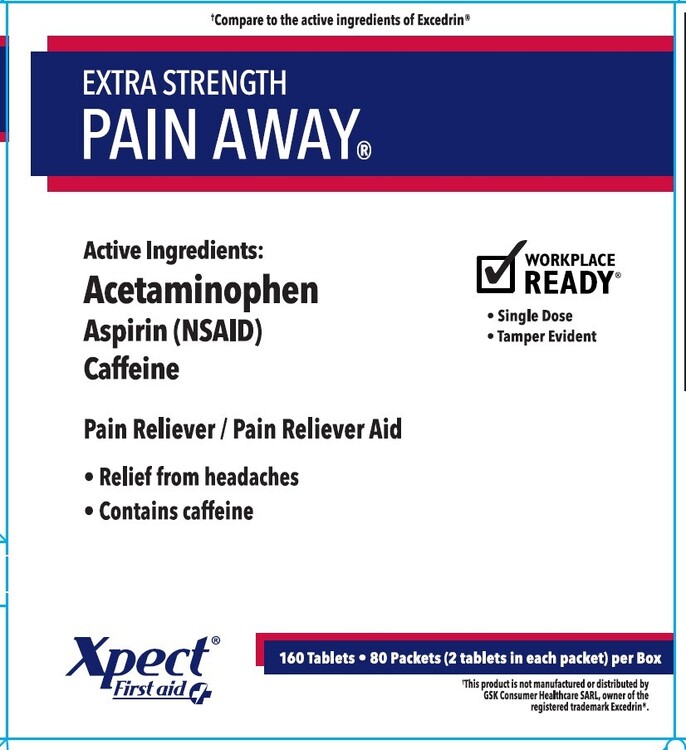 DRUG LABEL: Xpect Pain Away Extra Strength
NDC: 42961-234 | Form: TABLET
Manufacturer: Cintas Corporation
Category: otc | Type: HUMAN OTC DRUG LABEL
Date: 20250924

ACTIVE INGREDIENTS: ACETAMINOPHEN 250 mg/1 1; ASPIRIN 250 mg/1 1; CAFFEINE 65 mg/1 1
INACTIVE INGREDIENTS: STARCH, CORN; CROSPOVIDONE; HYPROMELLOSE, UNSPECIFIED; MICROCRYSTALLINE CELLULOSE; POVIDONE; PROPYLENE GLYCOL; SODIUM LAURYL SULFATE; SODIUM STARCH GLYCOLATE TYPE A; STEARIC ACID; TITANIUM DIOXIDE

Xpect Pain Away Extra Strength

Active ingredients (in each tablet)

Acetaminophen 250 mg

Aspirin 250 mg (NSAID)*

Caffeine 65 mg

*nonsteroidal anti-inflammatory drug

Purpose

Pain reliever

Pain reliever

Pain reliever aid

Uses

- temporarily relieves minor aches and pains due to: • a cold • toothache • headache • muscular aches • arthritis • premenstrual and menstrual cramps

Warnings

Reye's syndrome: Children and teenagers who have or are recovering from chicken pox or flu-like symptoms should not use this product. When using this product, if changes in bahavior with nausea and vomiting occur, consult a doctor becuase these symptoms could be an early sign of Reye's syndrome, a rare but serious illness.

Allergy alert: Aspirin may cause a severe allergic reaction which may include: • shock • facial swelling • hives • asthma (wheezing)

Allergy alert: Acetaminophen may cause severe skin reactions. Symptoms may include: • skin reddening •blisters • rash

If a skin reaction occurs, stop use and seek medical help right away.

Liver warning: This product contains acetaminophen. Severe liver damage may occur if you take

- more than 4,000 mg of acetaminophen in 24 hours
- with other drugs containing acetaminophen
- 3 or more alcoholic drinks every day while using this product

Stomach bleeding warning: This product contains an NSAID, which may cause severe stomach bleeding. The chance is higher if you

- have had stomach ulcers or bleeding problems
- take a blood thinning (anticoagulant) or steroid drug
- take other drugs containing prescription or nonprescription NSAIDs [aspirin, ibuprofen, naproxen, or others]
- have 3 or more alcoholic drinks every day while using this product
- are age 60 or older
- take more or for a longer time than directed

Caffeine warning: The recommended dose of this product contains about as much caffeine as a cup of coffee. Limit the use of caffeine-containing medications, foods, or beverages while taking this product because too much caffeine may cause nervousness, irritability, sleeplessness, and occasionally, rapid heart beat.

Do not use

- if you have ever had an allergic reaction to acetaminophen, aspirin, or any other pain reliever/fever reducer
- with any other drug containing acetaminophen (prescription or nonprescription). If you are not sure whether a drug contains acetaminophen, ask a doctor or pharmacist
- if you have ever had an allergic reaction to this product or any of its ingredients

Ask a doctor before use if

- you have liver disease
- you have asthma
- stomach bleeding warning applies to you
- you have a history of stomach problems, such as heartburn
- you are taking a diuretic
- you have high blood pressure, heart disease, liver cirrhosis, or kidney disease

Ask a doctor or pharmacist before use if you are

- taking a precription drug for diabetes, gout, or arthritis
- taking any other drug or are under a doctor's care for any serious condition

Stop use and ask a doctor if

- an allergic reaction occurs. Seek medical help right away
- you experience any of the following signs of stomach bleeding: • feel faint • have bloody or black stools • vomit blood • have stomach pain that does not get better
- ringing in the ears or a loss of hearing occurs
- redness or swelling is present
- pain gets worse or lasts for more than 10 days
- fever gets worse or lasts for more than 3 days
- new symptoms occur

These could be signs of a serious condition.

PREGNANCY OR BREAST FEEDING

If pregnant or breast-feeding, ask a health professional before use. It is especially important not to use aspirin at 20 weeks or later in pregnancy unless definitely directed to do so by a doctor because it may cause problems in the unborn child or complications during delivery.

Keep out of reach of children. In case of accidental overdose, get medical help or contact a Poison Control Center right away. Prompt medical attention is critical for adults as well as for children even if you do not notice any signs or symptoms.

Directions

- do not take more than directed
- drink a full glass of water with each dose
- adults and children 12 years and over: take 2 tablets every 6 hours. Do not take more than 8 tablets in 24 hours.
- children under 12 years: ask a doctor

Other information

- store at 25°C (77°F); excursions permitted between 15°-30°C (59°-86°F)
- see packet for expiration date and lot number

Inactive ingredients

corn starch, crospovidone, hypromellose, microcrystalline cellulose, povidone, propylene glycol, sodium lauryl sulfate, sodium starch glycolate, stearic acid, titanium dioxide

Questions?

1-877-973-2811 Monday-Friday 8:00 AM-5:00 PM

Principal Display Panel - 42961-234-04

†Compare to the active ingredients of Excedrin®

EXTRA STRENGTH PAIN AWAY®

Active Ingredients:

Acetaminophen

Aspirin (NSAID)

Caffeine

Pain Reliever / Pain Reliever Aid

- Relief from headaches
- Contains caffeine

Xpect® First aid

WORKPLACE READY®

- Single Dose
- Tamper Evident

80 Tablets • 40 Packets (2 tablets per packet) per Box

†This product is not manufactured or distributed by GSK Consumer Healthcare SARL, owner of the registered trademark Excedrin®.

Principal Display Panel - 42961-234-05

†Compare to the active ingredients of Excedrin®

EXTRA STRENGTH PAIN AWAY®

Active Ingredients:

Acetaminophen

Aspirin (NSAID)

Caffeine

Pain Reliever / Pain Reliever Aid

- Relief from headaches
- Contains caffeine

Xpect® First aid

WORKPLACE READY®

- Single Dose
- Tamper Evident

160 Tablets • 80 Packets (2 tablets per packet) per Box

†This product is not manufactured or distributed by GSK Consumer Healthcare SARL, owner of the registered trademark Excedrin®.